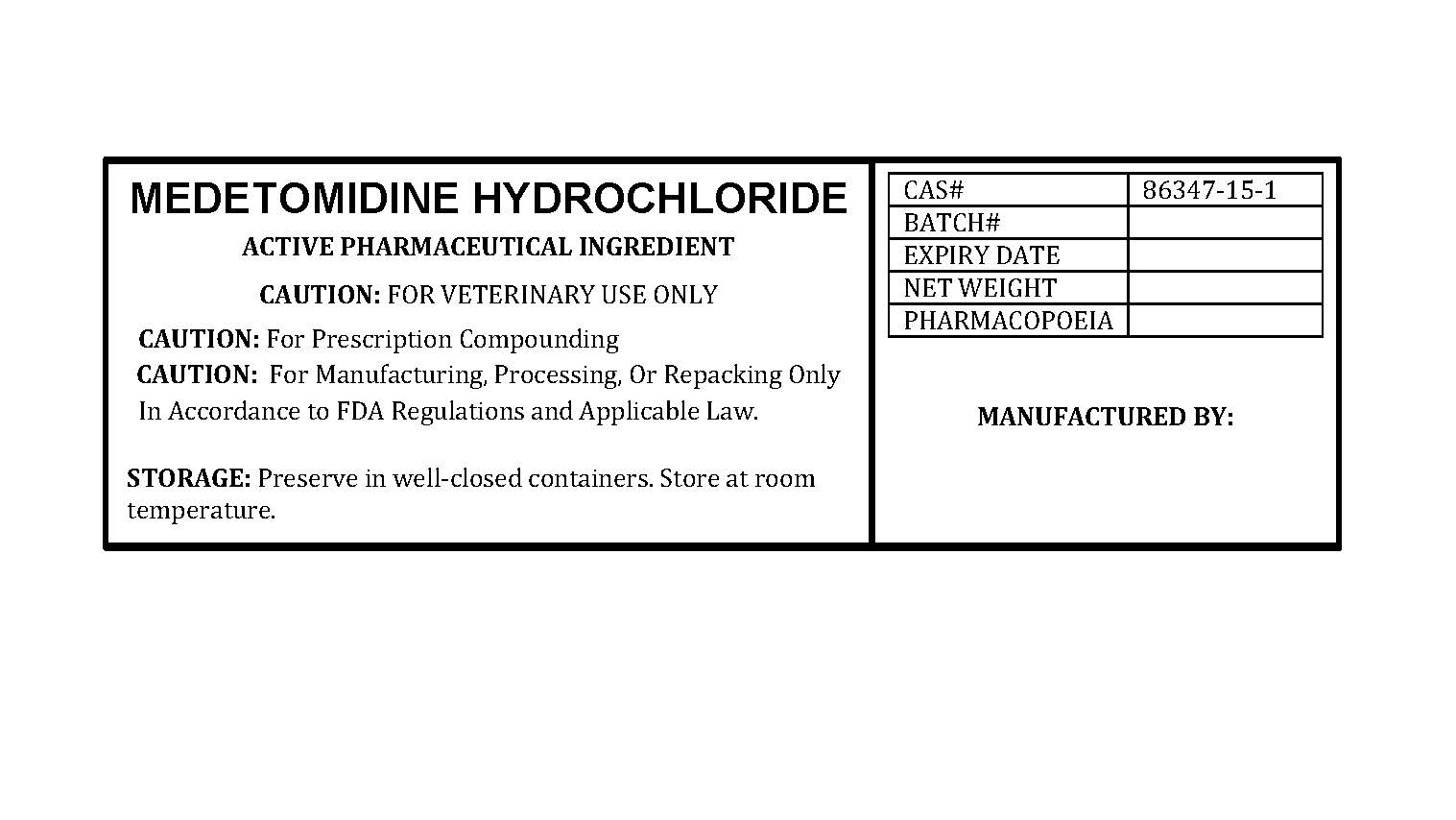 DRUG LABEL: MEDETOMIDINE HYDROCHLORIDE
NDC: 86184-242 | Form: POWDER
Manufacturer: MAEDA INC
Category: other | Type: BULK INGREDIENT - ANIMAL DRUG
Date: 20260216

ACTIVE INGREDIENTS: MEDETOMIDINE HYDROCHLORIDE 1 g/1 g

MEDETOMIDINE HYDROCHLORIDE

PACKAGE LABEL

medetomidinehydrochloridelabelfile.jpg